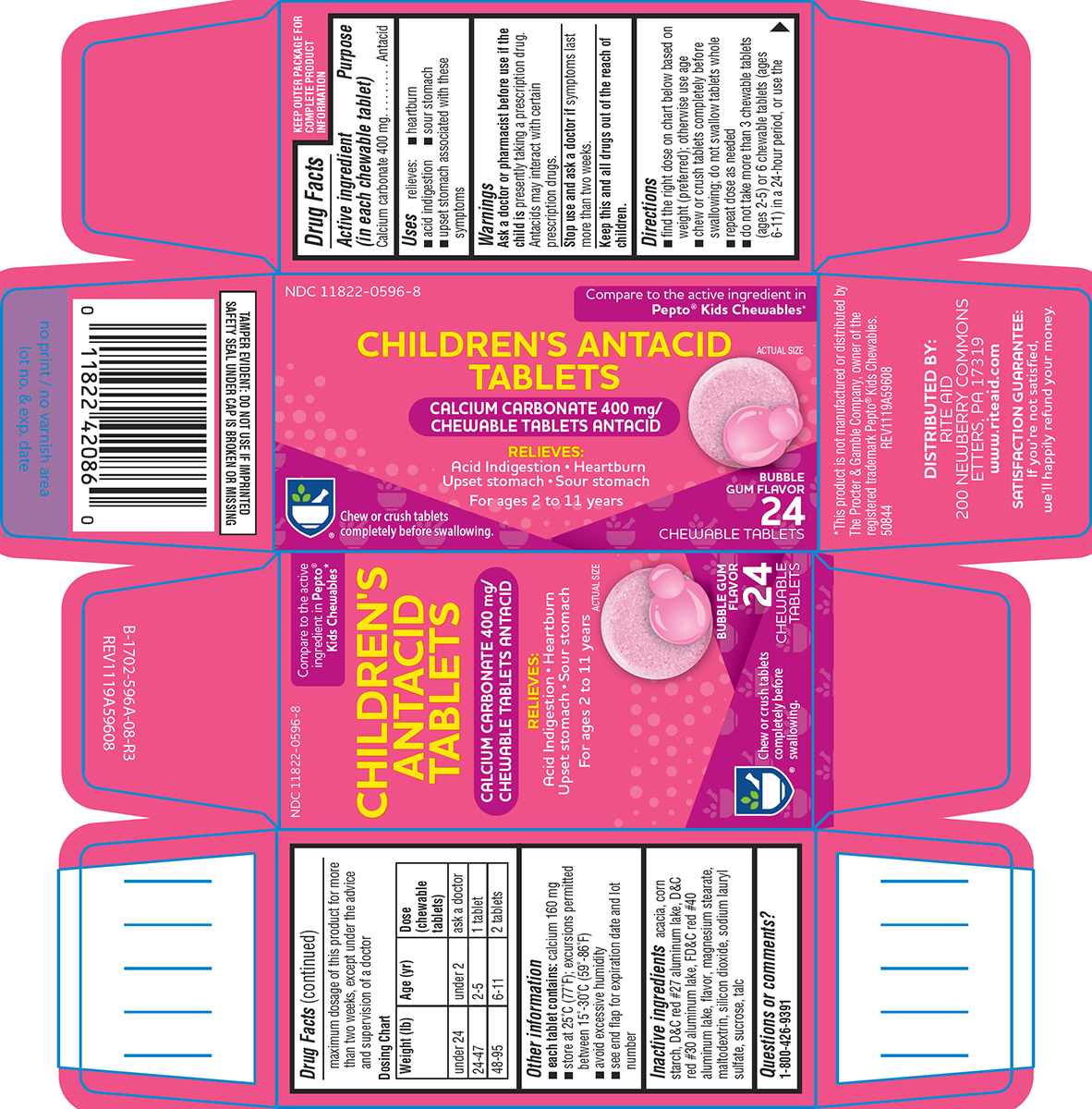 DRUG LABEL: Childrens Antacid
NDC: 11822-0596 | Form: TABLET, CHEWABLE
Manufacturer: Rite Aid Corporation
Category: otc | Type: HUMAN OTC DRUG LABEL
Date: 20250607

ACTIVE INGREDIENTS: CALCIUM CARBONATE 400 mg/1 1
INACTIVE INGREDIENTS: ACACIA; STARCH, CORN; D&C RED NO. 27 ALUMINUM LAKE; D&C RED NO. 30 ALUMINUM LAKE; FD&C RED NO. 40 ALUMINUM LAKE; MAGNESIUM STEARATE; MALTODEXTRIN; SILICON DIOXIDE; SODIUM LAURYL SULFATE; SUCROSE; TALC

Rite Aid 44-596A

Active ingredient (in each chewable tablet)

Calcium carbonate 400 mg

Purpose

Antacid

Uses

relieves:

- heartburn
- acid indigestion
- sour stomach
- upset stomach associated with these symptoms

Warnings

Ask a doctor or pharmacist before use if the child is

presently taking a prescription drug. Antacids may interact with certain prescription drugs.

Stop use and ask a doctor if

symptoms last more than two weeks.

Directions

- find the right dose on chart below based on weight (preferred); otherwise use age
- chew or crush tablets completely before swallowing; do not swallow tablets whole
- repeat dose as needed
- do not take more than 3 chewable tablets (ages 2-5) or 6 chewable tablets (ages 6-11) in a 24-hour period, or use the maximum dosage of this product for more than two weeks, except under the advice and supervision of a doctor

Dosing Chart

Weight (lb) | Age (yr) | Dose (chewable tablets)
under 24 | under 2 | ask a doctor
24-47 | 2-5 | 1 tablet
48-95 | 6-11 | 2 tablets

Other information

- each tablet contains: calcium 160 mg
- store at 25°C (77°F); excursions permitted between 15°-30°C (59°-86°F)
- avoid excessive humidity
- see end flap for expiration date and lot number

Inactive ingredients

acacia, corn starch, D&C red #27 aluminum lake, D&C red #30 aluminum lake, FD&C red #40 aluminum lake, flavor, magnesium stearate, maltodextrin, silicon dioxide, sodium lauryl sulfate, sucrose, talc

Questions or comments?

1-800-426-9391

Principal display panel

NDC 11822-0596-8

Compare to the active ingredient in
Pepto® Kids Chewables*

CHILDREN'S ANTACID
TABLETS

CALCIUM CARBONATE 400 mg/
CHEWABLE TABLETS ANTACID

RELIEVES:
Acid Indigestion • Heartburn
Upset stomach • Sour stomach

For ages 2 to 11 years

ACTUAL SIZE

BUBBLE
GUM FLAVOR

24
CHEWABLE TABLETS

Chew or crush tablets
completely before swallowing.

TAMPER EVIDENT: DO NOT USE IF IMPRINTED
SAFETY SEAL UNDER CAP IS BROKEN OR MISSING

*This product is not manufactured or distributed by
The Procter & Gamble Company, owner of the
registered trademark Pepto® Kids Chewables.
50844 REV1119A59608

DISTRIBUTED BY:
RITE AID
200 NEWBERRY COMMONS
ETTERS, PA 17319
www.riteaid.com

SATISFACTION GUARANTEE:
If you’re not satisfied,
we’ll happily refund your money.

Rite Aid 44-596A